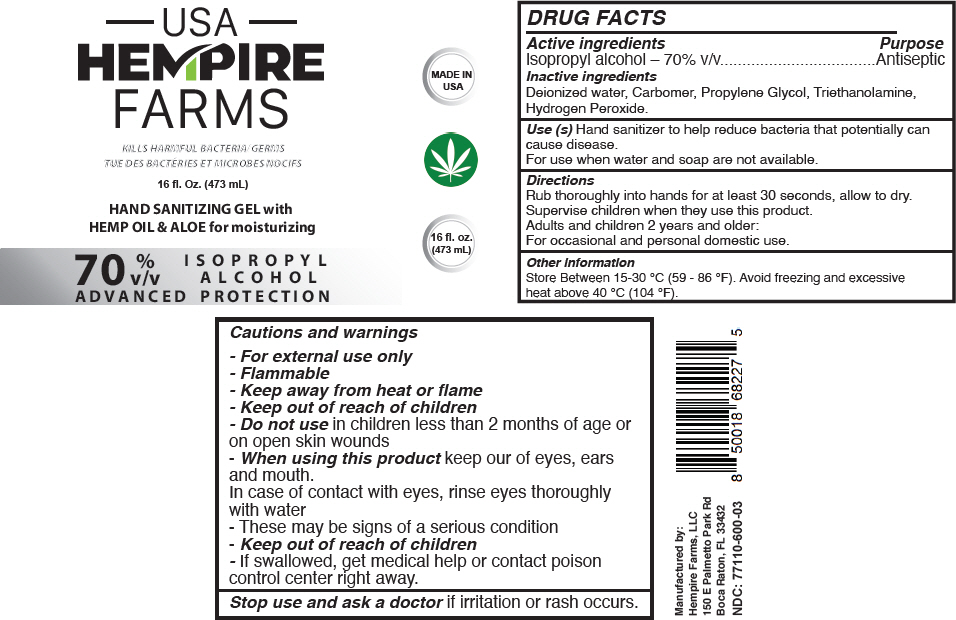 DRUG LABEL: HAND SANITIZING
NDC: 77110-600 | Form: GEL
Manufacturer: Biominerales Pharma
Category: otc | Type: HUMAN OTC DRUG LABEL
Date: 20200902

ACTIVE INGREDIENTS: Isopropyl alcohol 70 mL/100 mL
INACTIVE INGREDIENTS: Water; Carbomer Homopolymer, Unspecified Type; Propylene Glycol; Trolamine; Hydrogen Peroxide

HAND SANITIZING

DRUG FACTS

Active ingredients

Isopropyl alcohol – 70% v/v

Purpose

Antiseptic

Inactive ingredients

Deionized water, Carbomer, Propylene Glycol, Triethanolamine, Hydrogen Peroxide.

Use (s)

Hand sanitizer to help reduce bacteria that potentially can cause disease.

For use when water and soap are not available.

Directions

Rub thoroughly into hands for at least 30 seconds, allow to dry.

Supervise children when they use this product.

Adults and children 2 years and older:

For occasional and personal domestic use.

Other information

Store Between 15-30 °C (59 - 86 °F). Avoid freezing and excessive heat above 40 °C (104 °F).

Cautions and warnings

- For external use only
- Flammable
- Keep away from heat or flame
- Keep out of reach of children

- Do not use in children less than 2 months of age or on open skin wounds

- When using this product keep our of eyes, ears and mouth.

In case of contact with eyes, rinse eyes thoroughly with water

- These may be signs of a serious condition

- Keep out of reach of children
- If swallowed, get medical help or contact poison control center right away.

Stop use and ask a doctor if irritation or rash occurs.

Manufactured by:
Hempire Farms, LLC
150 E Palmetto Park Rd
Boca Raton, FL 33432

PRINCIPAL DISPLAY PANEL - 473 mL Container Label

USA
HEMPIRE
FARMS

MADE IN
USA

KILLS HARMFUL BACTERIA/GERMS

16 fl. Oz. (473 mL)

HAND SANITIZING GEL with
HEMP OIL & ALOE for moisturizing

16 fl. oz.
(473 mL)

70 %
v/v
ADVANCED

ISOPROPYL
ALCOHOL
PROTECTION